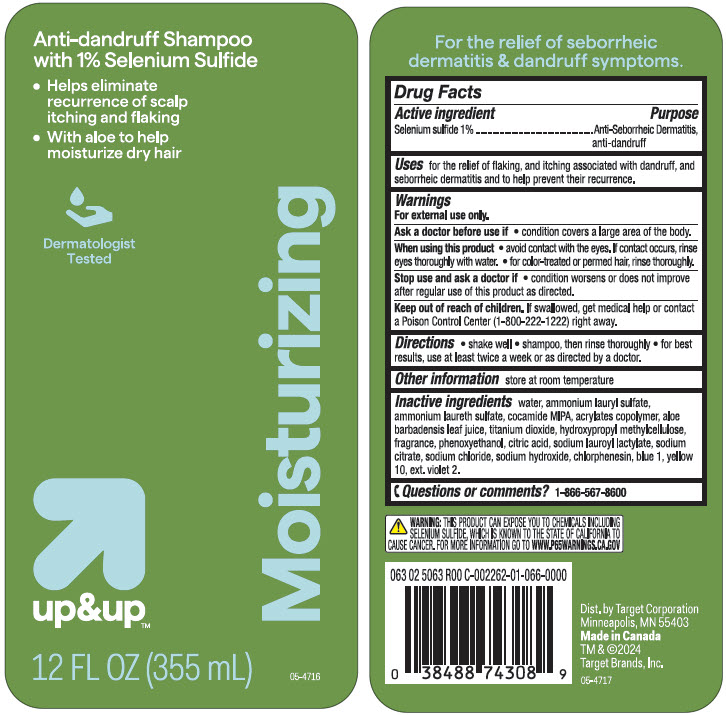 DRUG LABEL: up and up Moisturizing Anti-dandruff
NDC: 82442-308 | Form: SHAMPOO
Manufacturer: TARGET CORPORATION
Category: otc | Type: HUMAN OTC DRUG LABEL
Date: 20240510

ACTIVE INGREDIENTS: SELENIUM SULFIDE 10 mg/1 mL
INACTIVE INGREDIENTS: Water; AMMONIUM LAURETH-5 SULFATE; Ammonium Lauryl Sulfate; COCO MONOISOPROPANOLAMIDE; BUTYL ACRYLATE/METHYL METHACRYLATE/METHACRYLIC ACID COPOLYMER (18000 MW); ALOE VERA LEAF; Titanium Dioxide; HYPROMELLOSE, UNSPECIFIED; Phenoxyethanol; CITRIC ACID MONOHYDRATE; Sodium Lauroyl Lactylate; SODIUM CITRATE, UNSPECIFIED FORM; Sodium Chloride; Sodium Hydroxide; Chlorphenesin; FD&C BLUE NO. 1; D&C YELLOW NO. 10; EXT. D&C VIOLET NO. 2

up&up™ Moisturizing Anti-dandruff Shampoo
Anti-dandruff, anti-seborrheic dermatitis, anti-psoriasis

Drug Facts

Active ingredient

Selenium sulfide 1%

Purpose

Anti-Seborrheic Dermatitis, anti-dandruff

Uses

for the relief of flaking, and itching associated with dandruff, and seborrheic dermatitis and to help prevent recurrence.

Warnings

For external use only.

Ask a doctor before use if

- condition covers a large area of the body.

When using this product

- avoid contact with the eyes. If contact occurs, rinse eyes thoroughly with water.
- for color-treated or permed hair, rinse thoroughly.

Stop use and ask a doctor if

- condition worsens or does not improve after regular use of this product as directed.

Keep out of reach of children. If swallowed, get medical help or contact a Poison Control Center (1-800-222-1222) right away.

Directions

- shake well
- shampoo, then rinse thoroughly
- for best results, use at least twice a week or as directed by a doctor.

Other information

- store at room temperature

Inactive ingredients

water, ammonium lauryl sulfate, ammonium laureth sulfate, cocamide MIPA, acrylates copolymer, aloe barbadensis leaf juice, titanium dioxide, hydroxypropyl methylcellulose, fragrance, phenoxyethanol, citric acid, sodium lauroyl lactylate, sodium citrate, sodium chloride, sodium hydroxide, chlorphenesin, blue 1, yellow 10, ext. violet 2

Questions or comments?

1-866-567-8600

Dist. by Target Corporation
Minneapolis, MN 55403

PRINCIPAL DISPLAY PANEL - 355 mL Bottle Label

Anti-dandruff Shampoo
with 1% Selenium Sulfide

- Helps eliminate
  recurrence of scalp
  itching and flaking
- With aloe to help
  moisturize dry hair

Dermatologist
Tested

up&up™

12 FL OZ (355 mL)

Moisturizing

05-4716